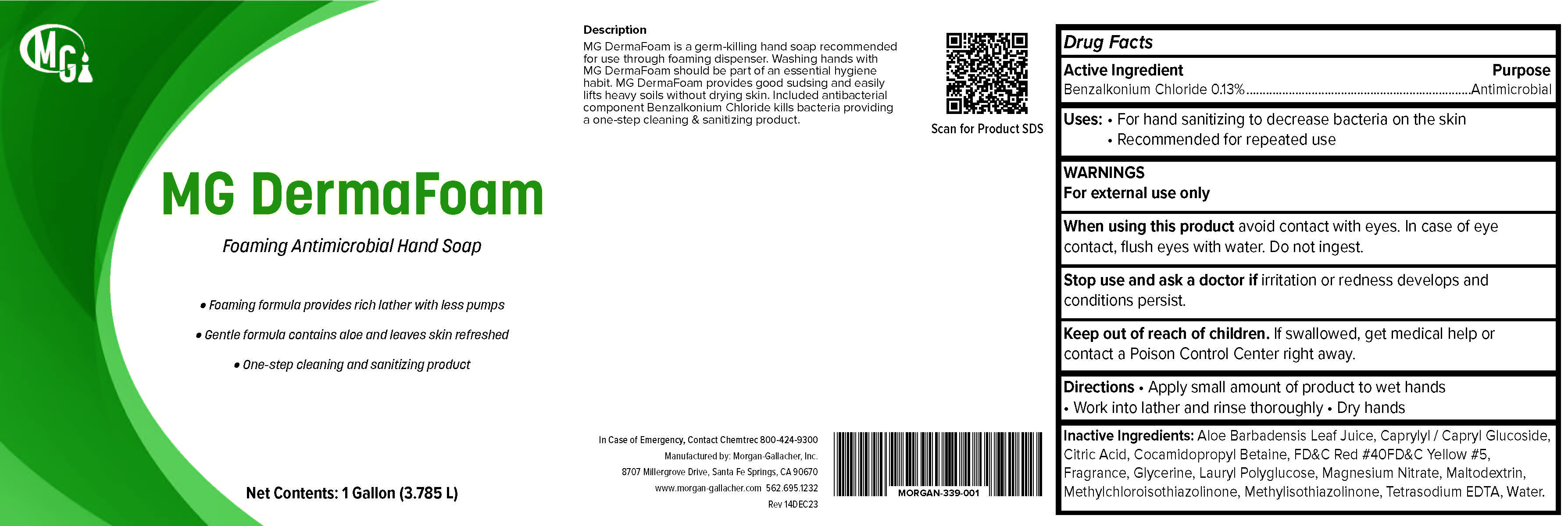 DRUG LABEL: MG DermaFoam
NDC: 50241-339 | Form: LIQUID
Manufacturer: Morgan Gallacher Inc. DBA Custom Chemical Formulators Inc.
Category: otc | Type: HUMAN OTC DRUG LABEL
Date: 20251223

ACTIVE INGREDIENTS: BENZALKONIUM CHLORIDE 13 kg/100 kg
INACTIVE INGREDIENTS: ALOE VERA LEAF; CAPRYLYL/CAPRYL OLIGOGLUCOSIDE; ANHYDROUS CITRIC ACID; COCAMIDOPROPYL BETAINE; GLYCERIN; LAURYL GLUCOSIDE; MAGNESIUM NITRATE; MALTODEXTRIN; METHYLCHLOROISOTHIAZOLINONE; METHYLISOTHIAZOLINONE; FD&C RED NO. 40; EDETATE SODIUM; WATER; FD&C YELLOW NO. 5

MG DermaFoam

ACTIVE INGREDIENT

Benzalkonium Chloride ...........0.13%

Purpose

Antimicrobial

Uses

For hand sanitizing to decrease bacteria on the skin.

recommended for repeated use.

Warnings

For external use only.

When Using this Product

- Avoid contact with eyes.

- In case of eye contact, flush eyes with water. Do not ingest.

- Stop use and contact a doctor if irritation or redness develops

or if conditions persist.

Keep out of reach of children. If swallowed, get medical help

or contact a Poison Control Center immediately.

Directions

-Apply small amount of product to wet hands.

-Work into lather and rinse thoroughly, and dry hands.

Inactive Ingredients

Water, Cocamidopropyl Betaine, Caprylyl Glucoside, Glycerine, Tetrasodium EDTA, Benzisothiazol, Methylisothiozol, Fragrance, Citric Acid, Aloe Vera, Yellow #5, Red #40